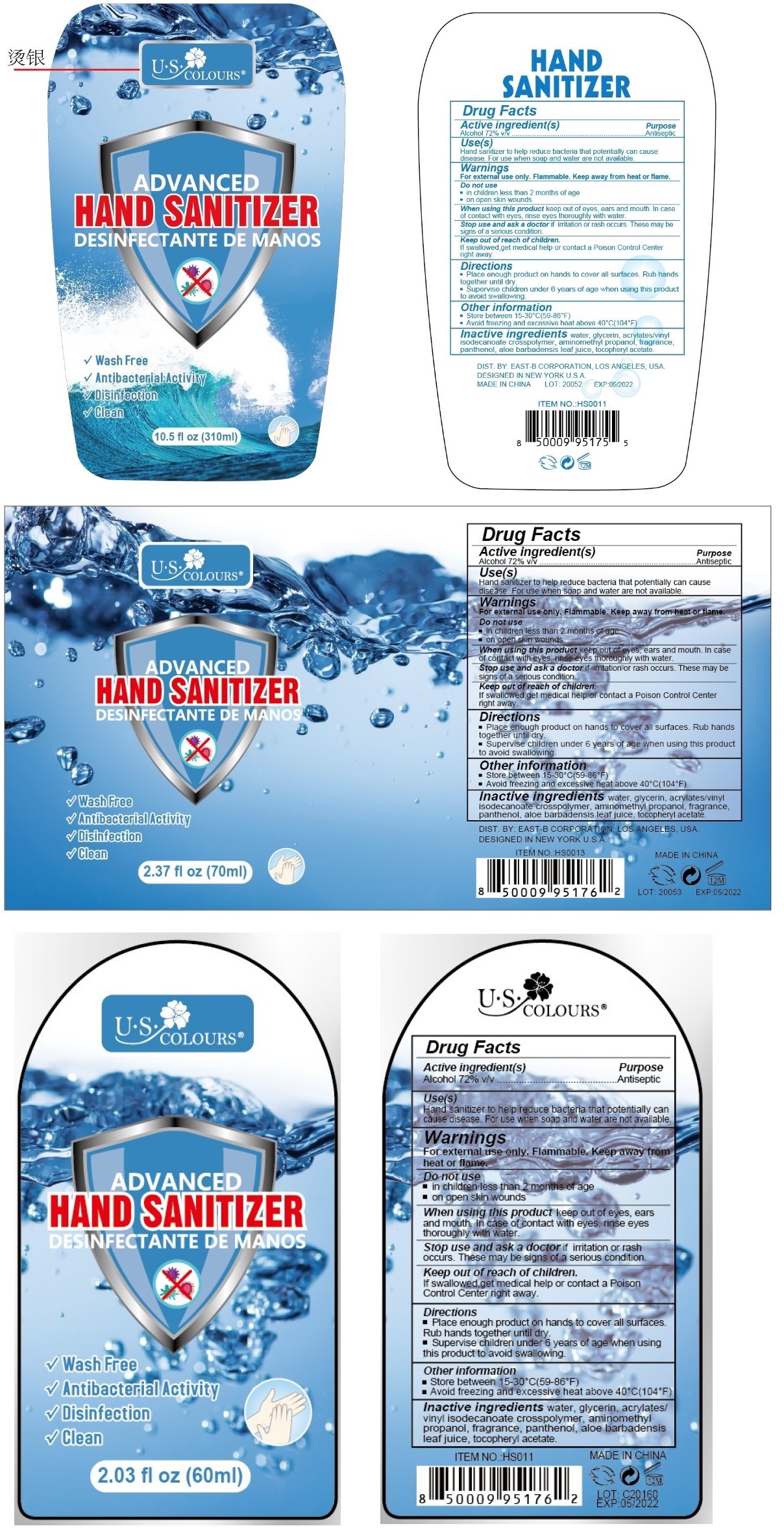 DRUG LABEL: U.S COLOURS
NDC: 74655-555 | Form: LIQUID
Manufacturer: East-B Corp.
Category: otc | Type: HUMAN OTC DRUG LABEL
Date: 20200522

ACTIVE INGREDIENTS: ALCOHOL 72 mL/100 mL
INACTIVE INGREDIENTS: WATER; GLYCERIN; AMINOMETHYLPROPANOL; PANTHENOL; ALOE VERA LEAF; .ALPHA.-TOCOPHEROL ACETATE

U.S COLOURS ADVANCED HAND SANITIZER

Active ingredient(s)

Alcohol 72% v/v

Purpose

Antiseptic

Use(s)

Hand sanitizer to help reduce bacteria that potentially can cause disease. For use when soap and water are not available.

Warnings

For external use only. Flammable. Keep away from heat or flame.

Do not use

▪ in children less than 2 months of age

▪ on open skin wounds

When using this product keep out of eyes, ears and mouth. In case of contact with eyes, rinse eyes thoroughly with water.

Stop use and ask a doctor if irritation or rash occurs. These may be signs of a serious condition.

Keep out of reach of children.

If swallowed, get medical help or contact a Poison Control Center right away.

Directions

▪ Place enough product on hands to cover all surfaces. Rub hands together until dry.

▪ Supervise children under 6 years of age when using this product to avoid swallowing.

Other information

▪ Store between 15-30°C (59-86°F)

▪ Avoid freezing and excessive heat above 40°C (104°F)

INACTIVE INGREDIENT

Inactive ingredients water, glycerin, acrylates/vinyl isodecanoate crosspolmer, aminomethyl propanol, fragrance, panthenol, aloe barbadensis leaf juice, tocopherol acetate

DESINFECTANTE DE MANOS

✓ Wash Free

✓ Antibacterial Activity

✓ Disinfection

✓ Clean

DIST. BY: EAST-B CORPORATION, LOS ANGELES, USA.

DESIGNED IN NEWYORK U.S.A.

MADE IN CHINA